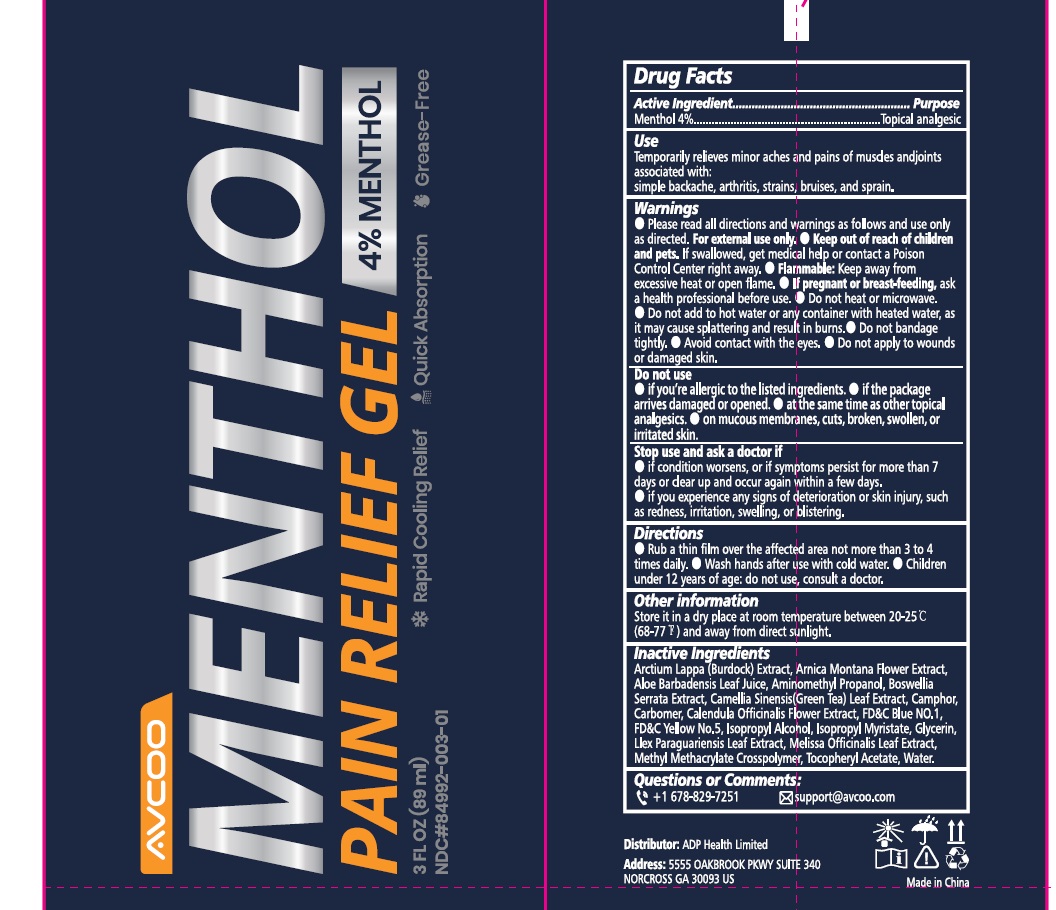 DRUG LABEL: AVCOO Pain Relief
NDC: 84992-003 | Form: GEL
Manufacturer: ADP Health Limited
Category: otc | Type: HUMAN OTC DRUG LABEL
Date: 20250219

ACTIVE INGREDIENTS: MENTHOL 4 g/100 mL
INACTIVE INGREDIENTS: WATER; ALOE VERA LEAF; GLYCERIN; AMINOMETHYLPROPANOL; ARCTIUM LAPPA WHOLE; ARNICA MONTANA FLOWER WATER; BOSWELLIA SERRATA WHOLE; CALENDULA OFFICINALIS FLOWER; CAMELLIA SINENSIS LEAF; CAMPHOR, (-)-; CARBOMER 934; FD&C BLUE NO. 1; FD&C YELLOW NO. 5; ILEX PARAGUARIENSIS LEAF; ISOPROPYL ALCOHOL; ISOPROPYL MYRISTATE; MELISSA OFFICINALIS LEAF; .ALPHA.-TOCOPHEROL ACETATE

84992-003 AVCOO 4% Menthol Pain relief

Active ingredient

Menthol 4%

Purpose

Topical Analgesic

Uses

Temporarily relieves minor aches and pains of sore muscles and joints associatedly with:

simple backaches, arthritis, strains, bruises, and sprain

Warnings

- Please read all directions and warnings as follows and use only as directed. For external use only.
- Flammable:Keep away from excessive heat and open flame
- Do not heat or microwave
- Do not add to hot water or any container with heated water, as it may cause splattering and resultin burns
- Do not bandage tightly
- Avoid contact with eyes
- Do not apply to wounds or damaged skin

Keep out of reach of children or pets. If swallowed, get medical help or contact a Poison Control Center right away

PREGNANCY

If pregnant or breast-feeding,ask a healthcare professional before use

Do not use

- if you are allergic to the listed ingredients
- if the package arrives damagedor opened
- at the same time as other topical analgesics
- on mucous membrances, cuts, broken, swollen, or irritated skin

Stop Use and Ask a Doctor

if condition worsens, or if syptoms persist for more than 7 days or clear up and occur again within a few days.

if you experience any signs of deterioration or skin injury, such as redness, irritation, swelling, and blistering

Directions

- Rub a thin film over the affected area no more than 3-4 times daily
- Wash hands after use with cold water
- Children under 12 years of age: do not use, consult a doctor

Other Information

- store in a dry place at room temperature between 20-25C (77-86F) and away from direct sunlight

Inactive ingredients

Arctium Lappa Extract, Arnica Montana Flower Extract, Aloe Barbadensis Leaf Juice, Aminomethyl Propanol, Boswellia Serrata Extrac, Calendula Officinalis Flower Extract, Camellia Sinensis Leaf Extract, Camphor, Carbomer, FD&C Blue No.1, FD&C Yellow No.5, Glycerin, Ilex Paraguariensis Leaf Extract, Isopropyl Alcohol, IsopropyI Myristate, Melissa Officinalis Leaf Extract, Methyl Methacrylate Crosspolymer, Tocopheryl Acetate, Water